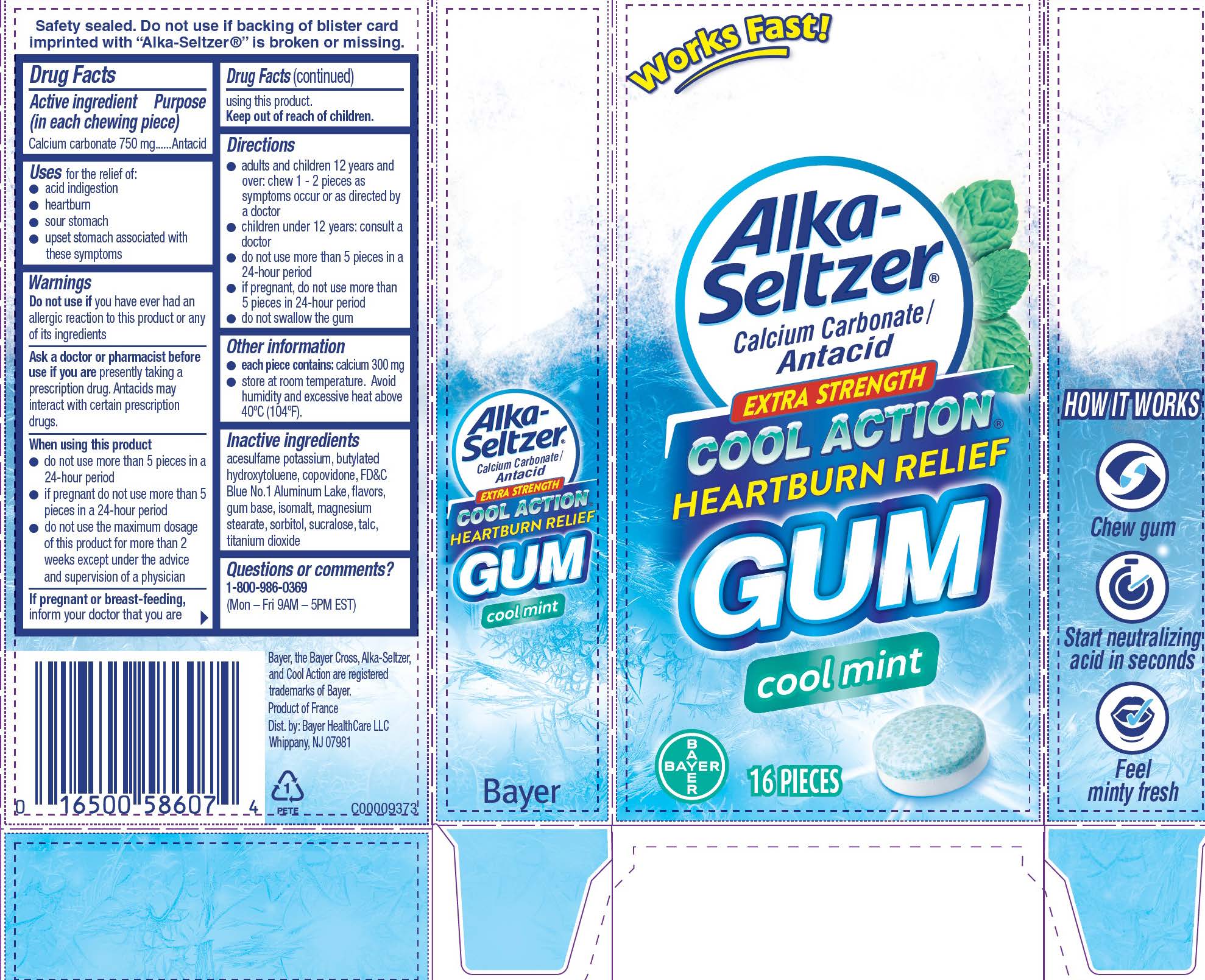 DRUG LABEL: Alka-Seltzer Cool Action Heartburn Relief
NDC: 0280-0001 | Form: GUM, CHEWING
Manufacturer: Bayer HealthCare LLC.
Category: otc | Type: HUMAN OTC DRUG LABEL
Date: 20251204

ACTIVE INGREDIENTS: CALCIUM CARBONATE 750 mg/1 1
INACTIVE INGREDIENTS: ISOMALT; SORBITOL; ACESULFAME POTASSIUM; TITANIUM DIOXIDE; SUCRALOSE; MAGNESIUM STEARATE; FD&C BLUE NO. 1--ALUMINUM LAKE; COPOVIDONE K25-31; BUTYLATED HYDROXYTOLUENE; TALC

Alka-Seltzer Cool Action Heartburn Relief Gum (mint) UI 1614451

Drug Facts

Active ingredient (in each chewing piece)

Calcium carbonate 750 mg

Purpose

Antacid

Uses

Uses for the relief of:

● acid indigestion ● heartburn ● sour stomach

● upset stomach associated with these symptoms

Warnings

Do not use if you have ever had an allergic reaction to this product or any of its ingredients

Ask a doctor or pharmacist before use if you are presently taking a prescription drug. Antacids may interact with certain prescription drugs.

When using this product
● do not use more than 5 pieces in a 24-hour period

● if pregnant do not use more than 5 pieces in a 24-hour period

● do not use the maximum dosage of this product for more

than 2 weeks except under the advice and supervision of a

physician

PREGNANCY OR BREAST FEEDING

If pregnant or breast-feeding, inform your doctor that you are using this product.

Keep out of reach of children.

Directions

● adults and children 12 years and over: chew 1 - 2 pieces as symptoms occur or as directed by a doctor

● children under 12 years: consult a doctor

● do not use more than 5 pieces in a 24-hour period

● if pregnant, do not use more than 5 pieces in 24-hour period

● do not swallow the gum

Other information

● each piece contains: calcium 300 mg

● store at room temperature. Avoid humidity and excessive heat above 40ºC (104ºF).

INACTIVE INGREDIENT

Inactive ingredients acesulfame potassium, butylated hydroxytoluene, copovidone, FD&C Blue No.1 Aluminum Lake, flavors, gum base, isomalt, magnesium stearate, sorbitol, sucralose, talc, titanium dioxide

Questions or comments? 1-800-986-0369

(Mon – Fri 9AM – 5PM EST)

Carton count 16 pieces

Works Fast!

Alka-Seltzer®

Calcium Carbonate/

Antacid

EXTRA STRENGTH

COOL ACTION

HEARTBURN RELIEF

GUM

cool mint

16 pieces